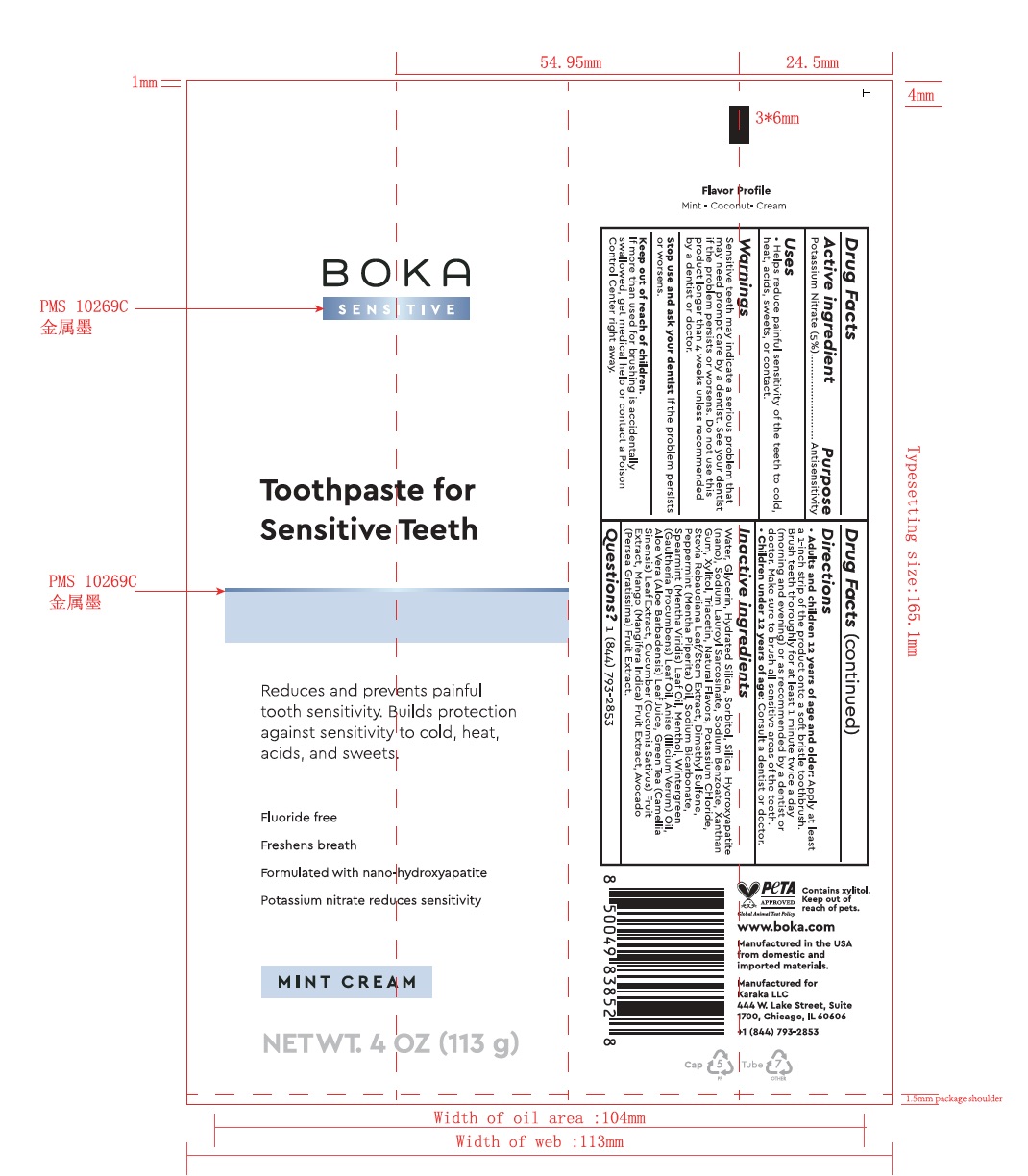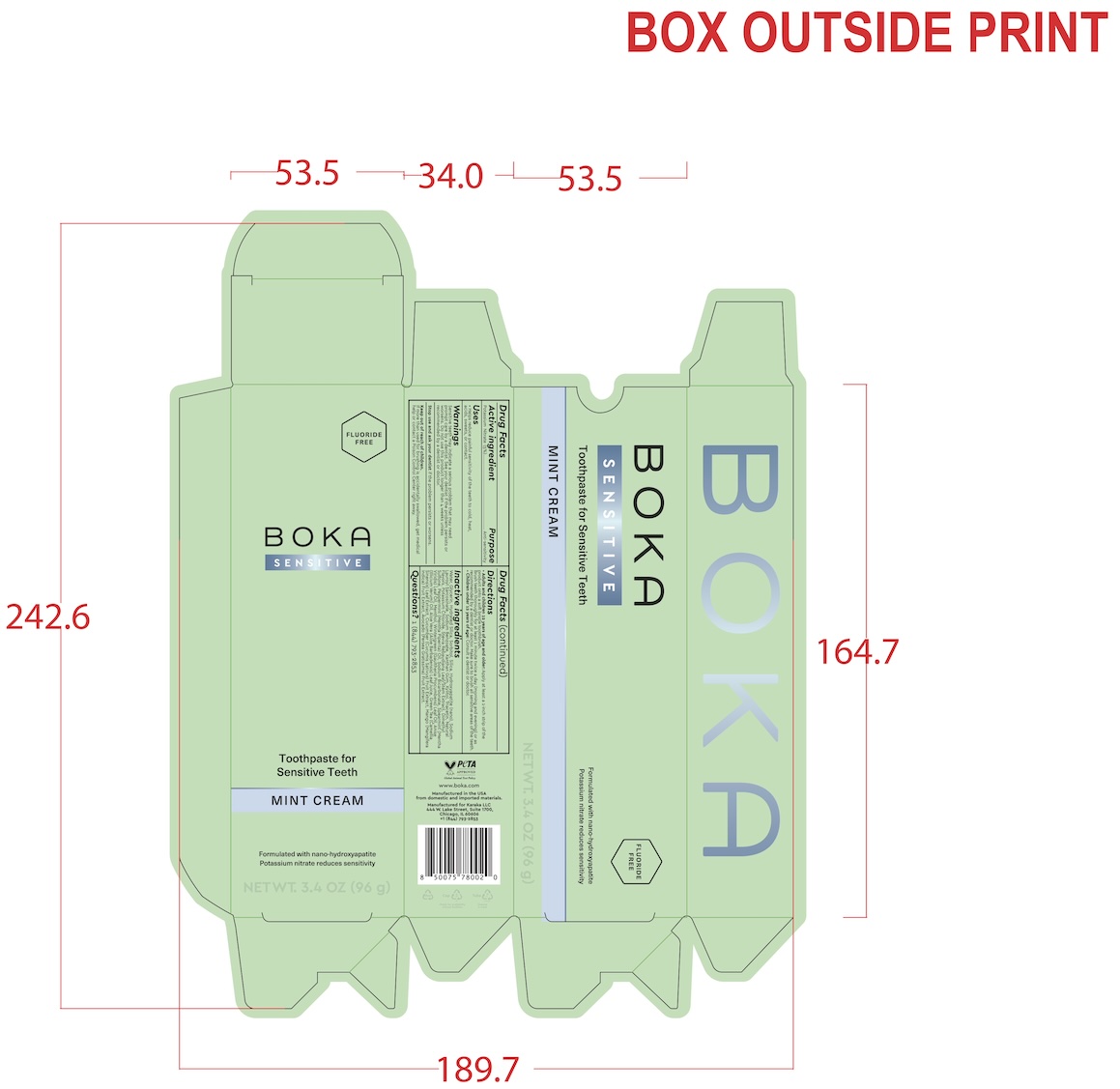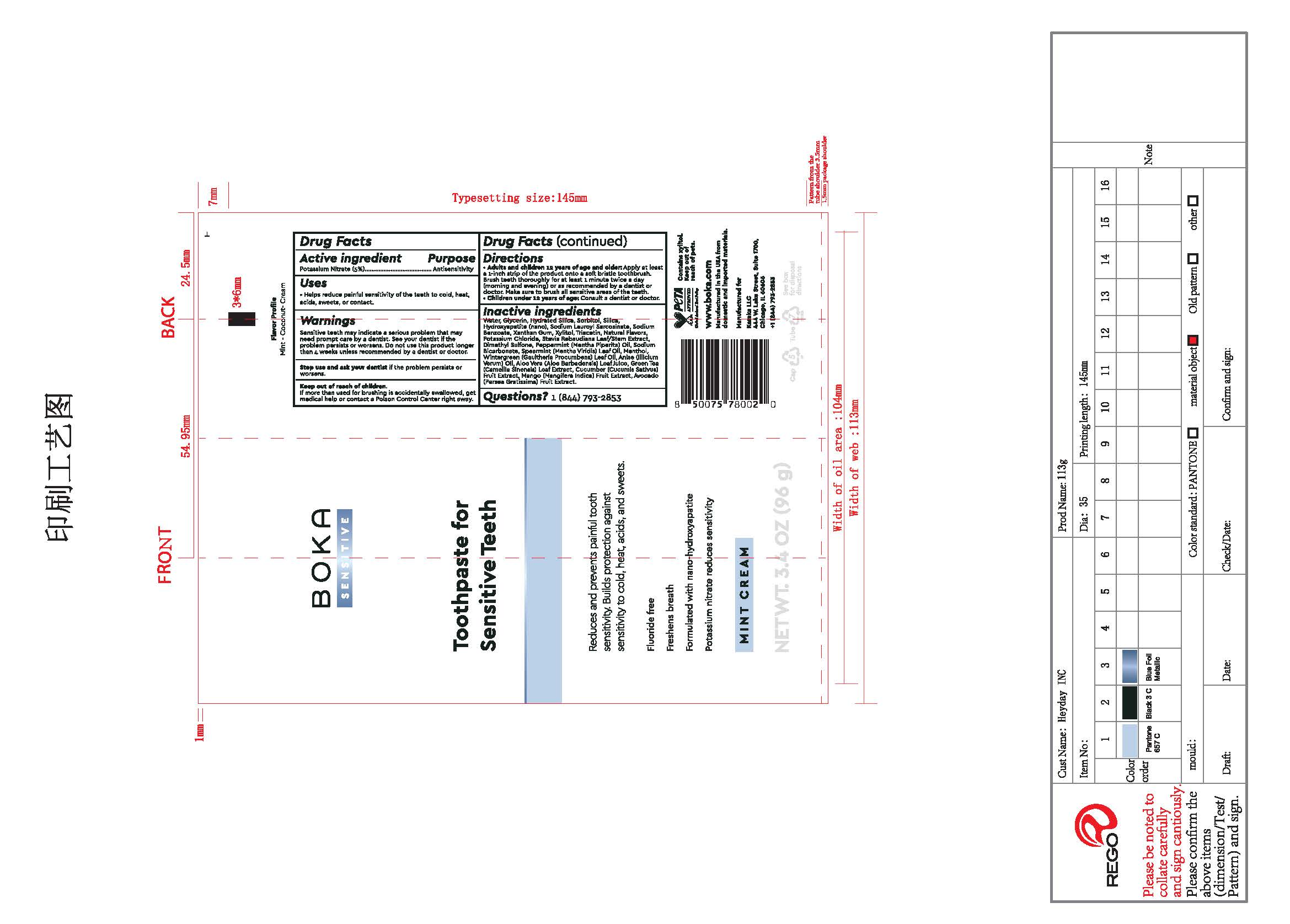 DRUG LABEL: Boka Sensitive
NDC: 87161-444 | Form: PASTE, DENTIFRICE
Manufacturer: Karaka LLC
Category: otc | Type: HUMAN OTC DRUG LABEL
Date: 20251023

ACTIVE INGREDIENTS: POTASSIUM NITRATE 5 g/100 g
INACTIVE INGREDIENTS: WATER; SILICA; MENTHA VIRIDIS (SPEARMINT) LEAF OIL; GAULTHERIA PROCUMBENS (WINTERGREEN) LEAF OIL; HYDRATED SILICA; SODIUM BENZOATE; GLYCERIN; SODIUM LAUROYL SARCOSINATE; MENTHA PIPERITA (PEPPERMINT) OIL; XYLITOL; XANTHAN GUM; GREEN TEA LEAF; SODIUM BICARBONATE; ALOE VERA LEAF JUICE; DIMETHYL SULFONE; SORBITOL; MANGIFERA INDICA (MANGO) FRUIT; AVOCADO; CUCUMIS SATIVUS (CUCUMBER) FRUIT; TRIACETIN; STAR ANISE OIL; STEVIA REBAUDIANA LEAF; MENTHOL; POTASSIUM CHLORIDE

Keep out of reach of children.

If more than used for brushing is accidentally swallowed, get medical help or contact a Poison Control Center right away.

PURPOSE

Antisensitivty

INACTIVE INGREDIENT

Water, Glyercin, Hydrated Silica, Sorbitol, Silica, Hydroxyapatite (nano), Sodium Lauroyl Sarcosinate, Sodium Benzoate, Xantham Gum, Xylitol, Triacertin, Flavors, Potassium Chloride, Stevia Rebaudiana Leaf/Stem Extract, Dimethyl Sulfone, Peppermint (Mentha Piperita) Oil, Sodium Bicarbonate, Spearmint (Mentha Viridis) Leaf Oil, Menthol, Wintergreen (Gaulteria Procumbens) Leaf Oil, Anise (illicium Verum) Oil, Aloe Vera (Aloe Barbadensis) Leaf Juice, Green Tea (Camellia Sinensis) Leaf Extract, Cucumber (Cucumis Sativus) Fruit Extract, Mango (Mangifera Indica) Fruit Extract, Avocado (Persea Gratissma) Fruit Extract

DOSAGE AND ADMINISTRATION

Adults and children 12 years of age and older:Apply at least a 1-inch strip of the product onto a soft-bristled toothbrush. Brush teeth thoroughly for at least 1 minute twice a day (morning and evening), or as recommended by a dentist or doctor. Make sure to brush all sensitive areas of the teeth.

Children under 12 years: Consult a dentist or doctor.

INDICATIONS AND USAGE

Helps reduce painful sensitivity of the teeth to cold, heat, acids, sweets, or contact.

WARNINGS

Sensitive teeth may indicate a serious problem that may need prompt care by a dentist. See your dentist if the problem persists or worsens. Do not use this product longer than 4 weeks unless recommended by a dentist or doctor.

Stop use and ask your dentistif the problem persists or worsens.

Keep out of reach of children.

If more than used for brushing is accidentally swallowed, get medical help or contact a Poison Control Center right away.